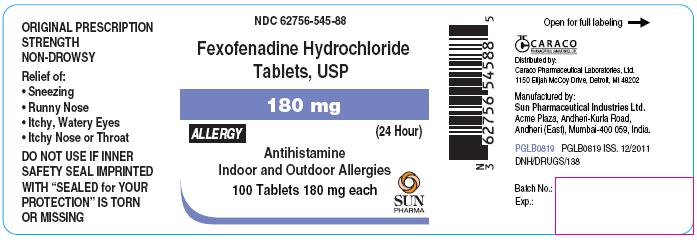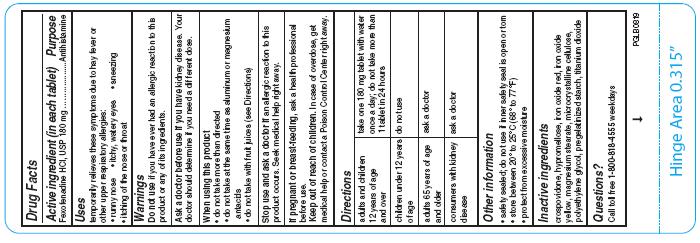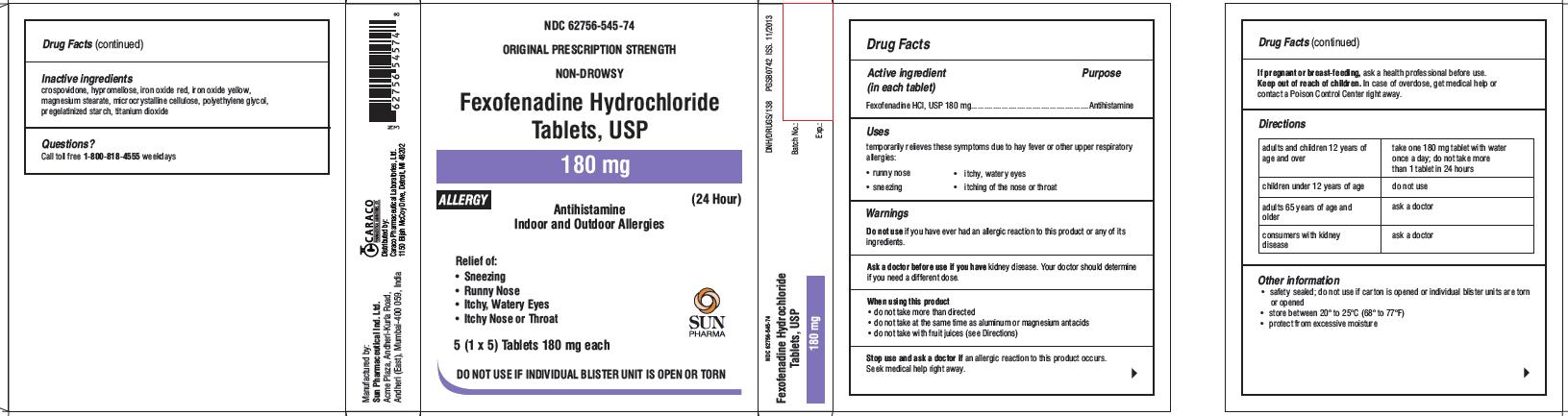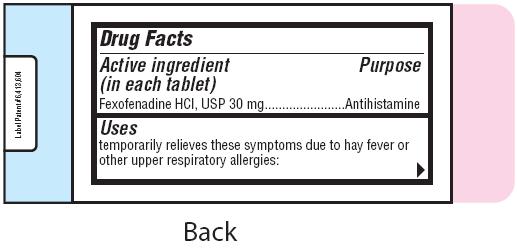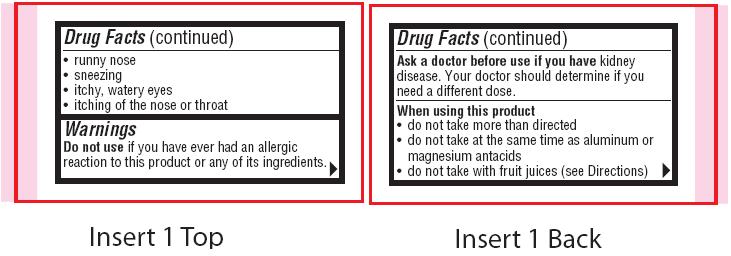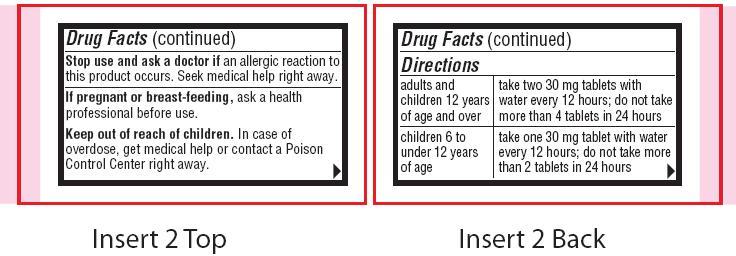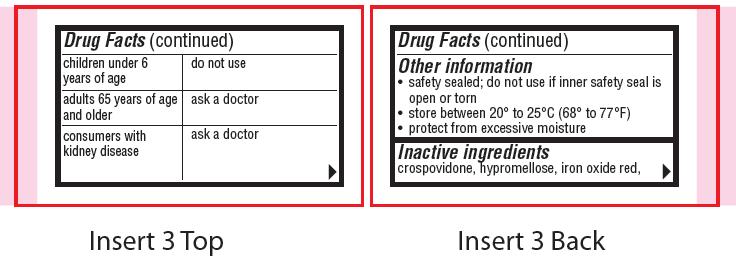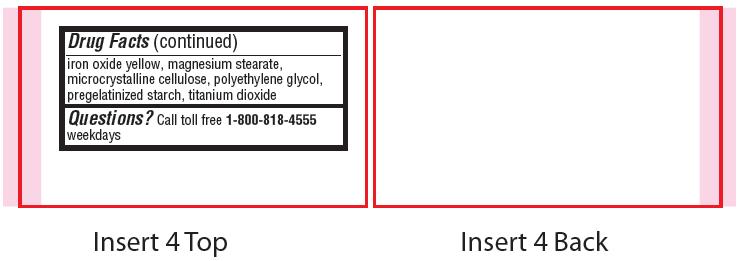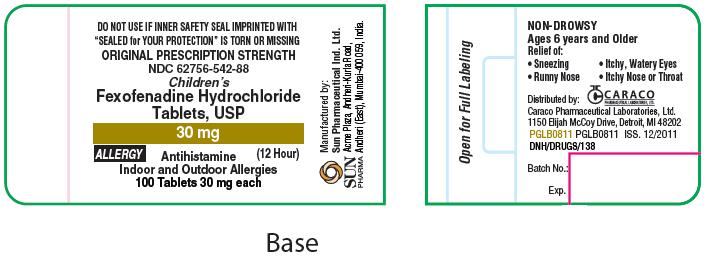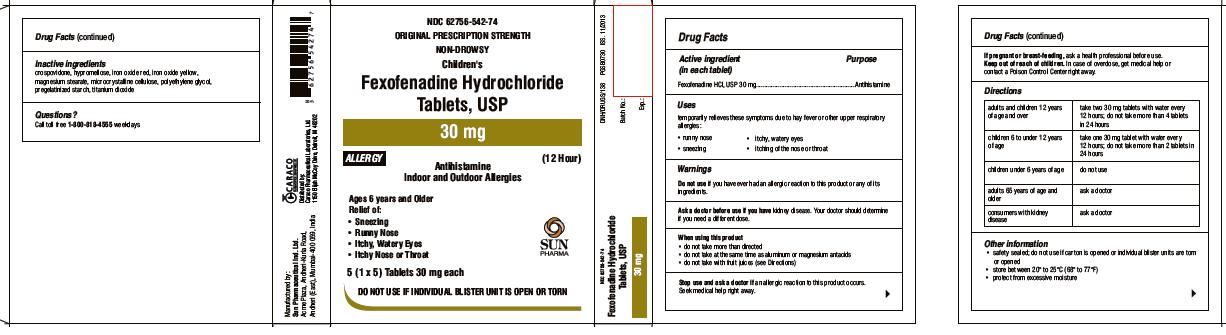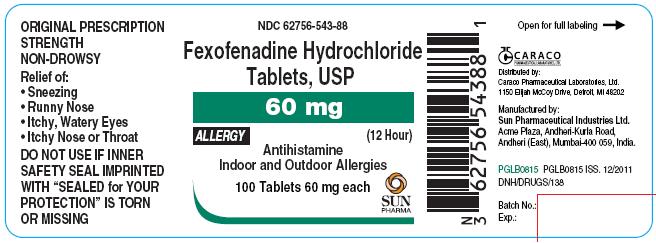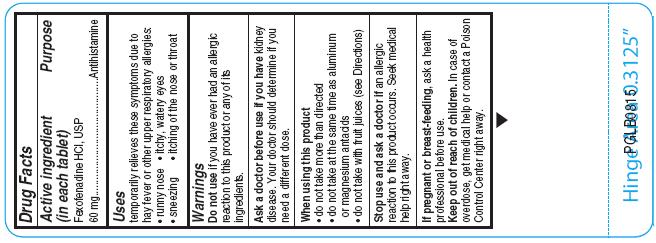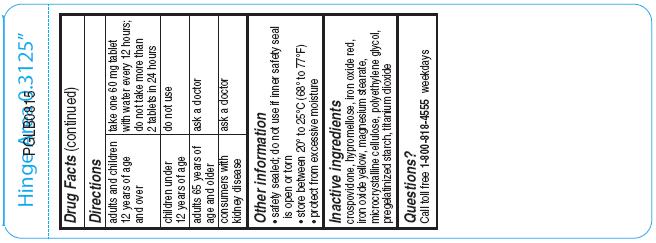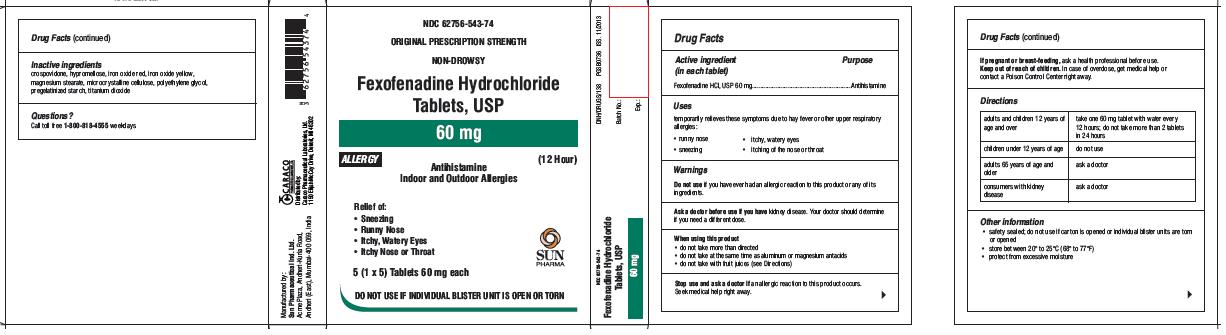 DRUG LABEL: FEXOFENADINE HYDROCHLORIDE
NDC: 62756-542 | Form: TABLET, FILM COATED
Manufacturer: Sun Pharmaceutical Industries, Inc.
Category: otc | Type: Human OTC Drug Label
Date: 20181026

ACTIVE INGREDIENTS: FEXOFENADINE HYDROCHLORIDE 30 mg/1 1
INACTIVE INGREDIENTS: CELLULOSE, MICROCRYSTALLINE; STARCH, CORN; CROSPOVIDONE; MAGNESIUM STEARATE; HYPROMELLOSE 2910 (6 MPA.S); TITANIUM DIOXIDE; POLYETHYLENE GLYCOL 400; FERRIC OXIDE RED; FERRIC OXIDE YELLOW

Fexofenadine Hydrochloride Tablets, USP

Active ingredient (in each tablet)

For 30 mg:
Fexofenadine HCl, USP 30 mg
For 60 mg:
Fexofenadine HCl, USP 60 mg
For 180 mg:
Fexofenadine HCl, USP 180 mg

Purpose

Antihistamine

Uses

temporarily relieves these symptoms due to hay fever or other upper respiratory allergies:

- runny nose
- sneezing
- itchy, watery eyes
- itching of the nose or throat

Warnings

Do not use if you have ever had an allergic reaction to this product or any of its ingredients.

Ask a doctor before use if you have

kidney disease. Your doctor should determine if you need a different dose.

When using this product

- do not take more than directed
- do not take at the same time as aluminum or magnesium antacids
- do not take with fruit juices (see Directions)

Stop use and ask doctor if

an allergic reaction to this product occurs. Seek medical help right away.

If pregnant or breast-feeding

ask a health professional before use.

Keep out of reach of children.

In case of overdose, get medical help or contact a Poison Control Center right away.

Directions

For 30mg:

adults and children 12 years of age and over | take two 30 mg tablets with water every 12 hours; do not take more than 4 tablets in 24 hours
children 6 to under 12 years of age | take one 30 mg tablet with water every 12 hours; do not take more than 2 tablets in 24 hours
children under 6 years of age | do not use
adults 65 years of age and older | ask a doctor
consumers with kidney disease | ask a doctor

For 60mg:

adults and children 12 years of age and over | take one 60 mg tablet with water every 12 hours; do not take more than 2 tablets in 24 hours
children under 12 years of age | do not use
adults 65 years of age and older | ask a doctor
consumers with kidney disease | ask a doctor

For 180mg:

adults and children 12 years of age and over | take one 180 mg tablet with water once a day; do not take more than 1 tablet in 24 hours
children under 12 years of age | do not use
adults 65 years of age and older | ask a doctor
consumers with kidney disease | ask a doctor

Other information

- safety sealed; do not use if inner safety seal is open or torn
- store between 20° to 25°C (68° to 77°F)
- protect from excessive moisture

Inactive ingredients

crospovidone, hypromellose, iron oxide red, iron oxide yellow, magnesium stearate, microcrystalline cellulose, polyethylene glycol, pregelatinized starch, titanium dioxide

Questions?

Call toll free 1-800-818-4555 weekdays

Principal Display Panel

For 30 mg Allergy:
ORIGINAL PRESCRIPTION STRENGTH
NDC 62756-542-88
Children's
Fexofenadine Hydrochloride Tablets, USP
30 mg
ALLERGY
(12 Hour)
Antihistamine
Indoor and Outdoor Allergies
100 Tablets 30 mg each
SUN PHARMA
For 60 mg Allergy:

NDC 62756-543-88
Fexofenadine Hydrochloride Tablets, USP
60 mg
ALLERGY
(12 Hour)
Antihistamine
Indoor and Outdoor Allergies
100 Tablets 60 mg each
SUN PHARMA

For 180 mg Allergy:
NDC 62756-545-88
Fexofenadine Hydrochloride Tablets, USP
180 mg
ALLERGY
(24 Hour)
Antihistamine
Indoor and Outdoor Allergies
100 Tablets 180 mg each
SUN PHARMA

Principal Display Panel

For 30 mg Allergy:
NDC 62756-542-74
ORIGINAL PRESCRIPTION STRENGTH
NON-DROWSY
Children's
Fexofenadine Hydrochloride Tablets, USP
30 mg
ALLERGY
(12 Hour)
Antihistamine
Indoor and Outdoor Allergies
Ages 6 years and Older
Relief of:
- Sneezing
- Runny Nose
- Itchy, Watery Eyes
- Itchy Nose or Throat
5 (1 x 5)Tablets 30 mg each
SUN PHARMA
DO NOT USE IF INDIVIDUAL BLISTER UNIT IS OPEN OR TORN

Principal Display Panel

For 60 mg Allergy:
NDC 62756-543-74
ORIGINAL PRESCRIPTION STRENGTH
NON-DROWSY
Fexofenadine Hydrochloride Tablets, USP
60 mg
ALLERGY
(12 Hour)
Antihistamine
Indoor and Outdoor Allergies
Relief of:
- Sneezing
- Runny Nose
- Itchy, Watery Eyes
- Itchy Nose or Throat
5 (1 x 5)Tablets 60 mg each
SUN PHARMA
DO NOT USE IF INDIVIDUAL BLISTER UNIT IS OPEN OR TORN

Principal Display Panel

For 180 mg Allergy:
NDC 62756-545-74
ORIGINAL PRESCRIPTION STRENGTH
NON-DROWSY
Fexofenadine Hydrochloride Tablets, USP
180 mg
ALLERGY
(24 Hour)
Antihistamine
Indoor and Outdoor Allergies
Relief of:
- Sneezing
- Runny Nose
- Itchy, Watery Eyes
- Itchy Nose or Throat
5 (1 x 5)Tablets 180 mg each
SUN PHARMA
DO NOT USE IF INDIVIDUAL BLISTER UNIT IS OPEN OR TORN